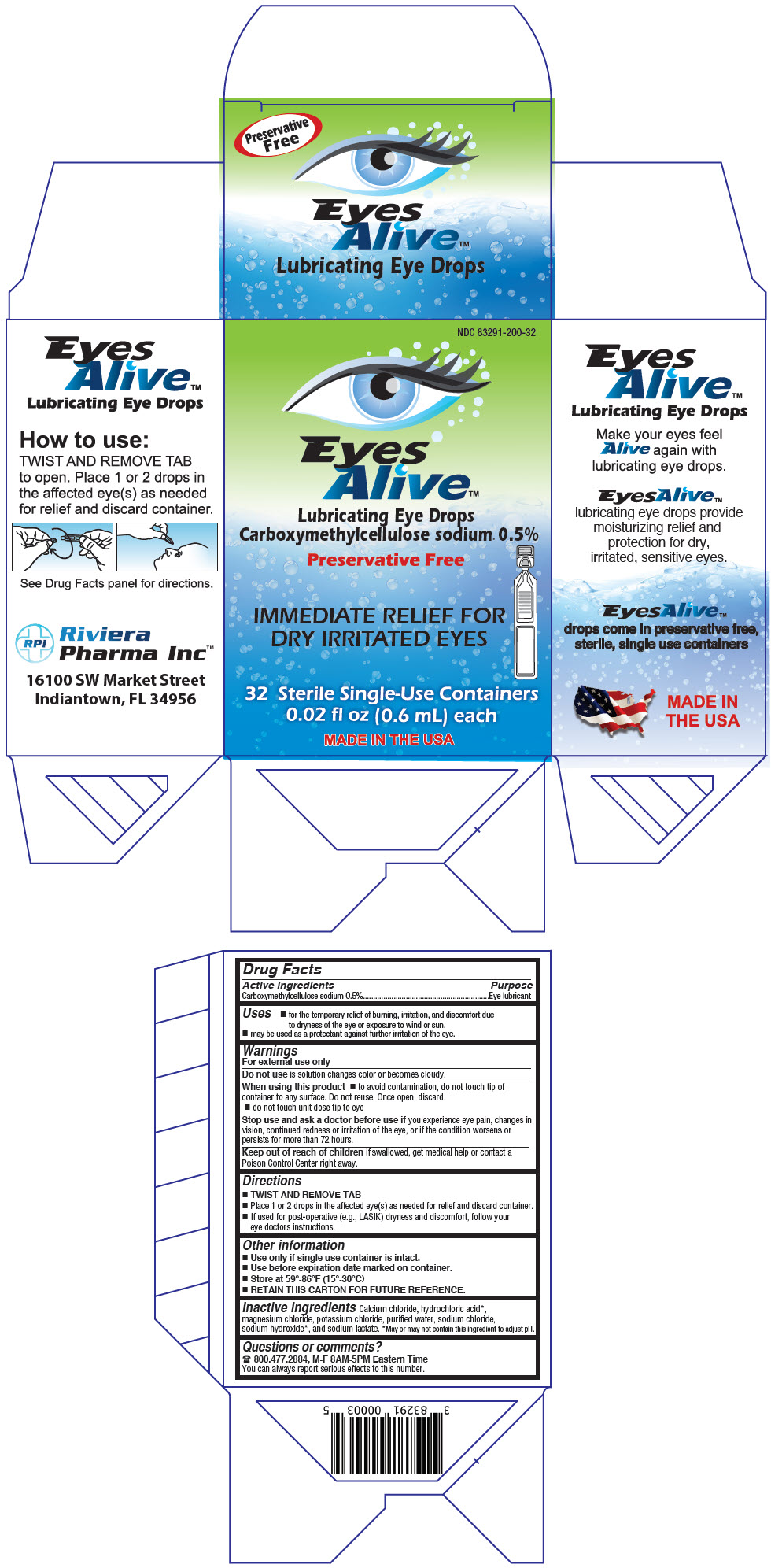 DRUG LABEL: Eyes Alive 
NDC: 83291-200 | Form: LIQUID
Manufacturer: RIVIERA PHARMA INC
Category: otc | Type: HUMAN OTC DRUG LABEL
Date: 20240531

ACTIVE INGREDIENTS: CARBOXYMETHYLCELLULOSE SODIUM, UNSPECIFIED 5 mg/1 mL
INACTIVE INGREDIENTS: CALCIUM CHLORIDE; HYDROCHLORIC ACID; MAGNESIUM CHLORIDE; POTASSIUM CHLORIDE; WATER; SODIUM CHLORIDE; SODIUM HYDROXIDE; SODIUM LACTATE

Eyes Alive™
Lubricating

Drug Facts

Active ingredients

Carboxymethylcellulose sodium 0.5%

Purpose

Eye lubricant

Uses

- for the temporary relief of burning, irritation, and discomfort due to dryness of the eye or exposure to wind or sun.
- may be used as a protectant against further irritation of the eye.

Warnings

For external use only

Do not use is solution changes color or becomes cloudy.

When using this product

- to avoid contamination, do not touch tip of container to any surface. Do not reuse. Once open, discard.
- do not touch unit dose tip to eye

Stop use and ask a doctor before use if you experience eye pain, changes in vision, continued redness or irritation of the eye, or if the condition worsens or persists for more than 72 hours.

Keep out of reach of children if swallowed, get medical help or contact a Poison Control Center right away.

Directions

- TWIST AND REMOVE TAB
- Place 1 or 2 drops in the affected eye(s) as needed for relief and discard container.
- If used for post-operative (e.g., LASIK) dryness and discomfort, follow your eye doctors instructions.

Other information

- Use only if single use container is intact.
- Use before expiration date marked on container.
- Store at 59°-86°F (15°-30°C)
- RETAIN THIS CARTON FOR FUTURE REFERENCE.

Inactive ingredients

Calcium chloride, hydrochloric acid [May or may not contain this ingredient to adjust pH.] , magnesium chloride, potassium chloride, purified water, sodium chloride, sodium hydroxide, and sodium lactate.

Questions or comments?

800.477.2884, M-F 8AM-5PM Eastern Time

You can always report serious effects to this number.

PRINCIPAL DISPLAY PANEL - 0.6 mL Container Carton

NDC 83291-200-32

Eyes
Alive™

Lubricating Eye Drops
Carboxymethylcellulose sodium 0.5%

Preservative Free

IMMEDIATE RELIEF FOR
DRY IRRITATED EYES

32 Sterile Single-Use Containers
0.02 fl oz (0.6 mL) each

MADE IN THE USA